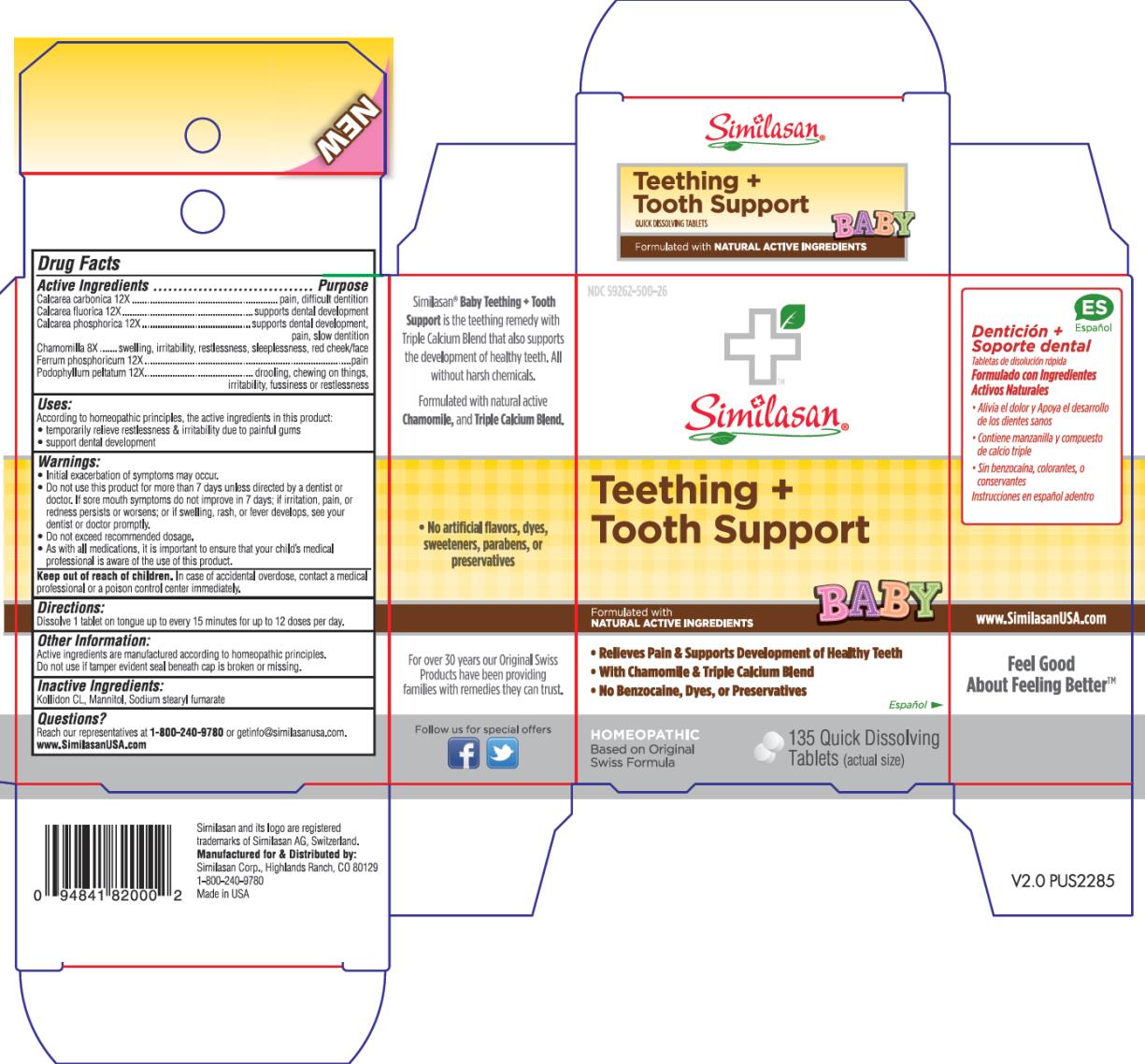 DRUG LABEL: Baby Teething Plus Tooth Support
NDC: 59262-500 | Form: TABLET, ORALLY DISINTEGRATING
Manufacturer: Similasan Corporation
Category: homeopathic | Type: HUMAN OTC DRUG LABEL
Date: 20140915

ACTIVE INGREDIENTS: OYSTER SHELL CALCIUM CARBONATE, CRUDE 12 [hp_X]/1 1; CALCIUM FLUORIDE 12 [hp_X]/1 1; TRIBASIC CALCIUM PHOSPHATE 12 [hp_X]/1 1; MATRICARIA RECUTITA 12 [hp_X]/1 1; FERROSOFERRIC PHOSPHATE 12 [hp_X]/1 1; PODOPHYLLUM 12 [hp_X]/1 1
INACTIVE INGREDIENTS: MANNITOL; SODIUM STEARYL FUMARATE

Baby Teething Plus Tooth Support

Drug Facts

Active Ingredient

Calcarea carbonica 12X

Purpose

pain, difficult dentition

Active Ingredient

Calcarea fluorica 12X

Purpose

supports dental development

Active Ingredient

Calcarea phosphorica 12X

Purpose

supports dental development, pain, slow dentition

Active Ingredient

Chamomilla 8X

Purpose

swelling, irritability, restlessness, sleeplessness, red cheek/face

Active Ingredient

Ferrum phosphoricum 12X

Purpose

fussiness or restlessness

Active Ingredient

Podophyllum peltatum 12X

Purpose

drooling, chewing on things, irritability

Uses:

According to the homeopathic principles, the active ingredients in this product:

- temporarily relieve restlessness & irritability due to painful gums
- support dental development

Warnings:

- Initial exacerbation of symptoms may occur.
- Do not use this product for more than 7 days unless directed by a dentist or doctor. If sore mouth symptoms do not improve in 7 days; if irritation, pain, or redness persists or worsens; or if swelling, rash, or fever develops, see your dentist or doctor promptly.
- Do not exceed recommended dosage.
- As with all medications, it is important to ensure that your child’s medical professional is aware of the use of this product.

Keep out of reach of children.

In case of accidental overdose, contact a medical professional or a poison control center immediately.

Directions:

Dissolve 1 tablet on tongue up to every 15 minutes for up to 12 doses per day.

Other Information:

Active ingredients are manufactured according to homeopathic principles.

Do not use if tamper evident seal beneath cap is broken or missing.

Inactive Ingredients:

Kollidon CL, Mannitol, Sodium stearyl fumarate

Questions?

Reach our representatives at 1-800-240-9780 or getinfo@similasanusa.com.

www.SimilasanUSA.com

PRINCIPAL DISPLAY PANEL

NDC 59262-500-26
Similasan®
Teething +
Tooth Support
BABY
135 Quick Dissolving
Tablets